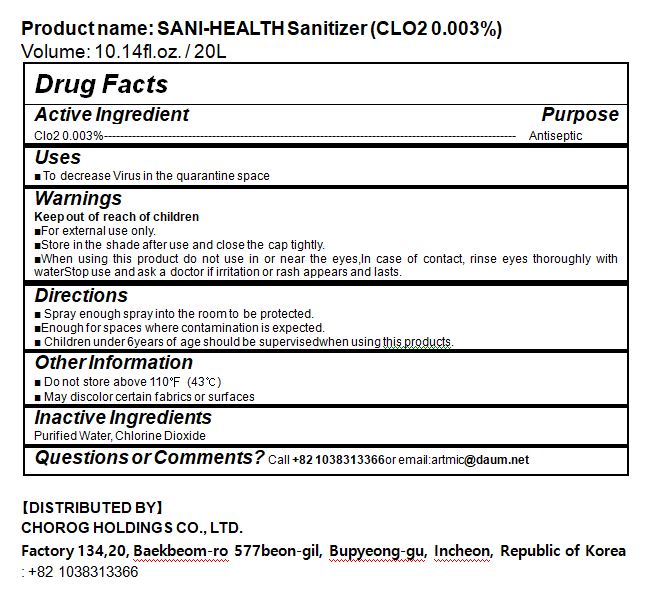 DRUG LABEL: SANI-HEALTH Sanitizer
NDC: 80998-0001 | Form: SPRAY
Manufacturer: Chorogholdings co., ltd.
Category: otc | Type: HUMAN OTC DRUG LABEL
Date: 20210327

ACTIVE INGREDIENTS: CHLORINE DIOXIDE 0.003 g/20000 mL
INACTIVE INGREDIENTS: WATER

80998-0001

ACTIVE INGREDIENT

chlorine dioxide

INACTIVE INGREDIENT

Water

PURPOSE

antiseptic

keep out of reach of the children

INDICATIONS AND USAGE

■ Spray enough spray into the room to be protected.

■Enough for spaces where contamination is expected.

■ Children under 6years of age should be supervisedwhen using this products.

WARNINGS

■For external use only.

■Store in the shade after use and close the cap tightly.

■When using this product do not use in or near the eyes,In case of contact, rinse eyes thoroughly with waterStop use and ask a doctor if irritation or rash appears and lasts.

DOSAGE AND ADMINISTRATION

for external use only